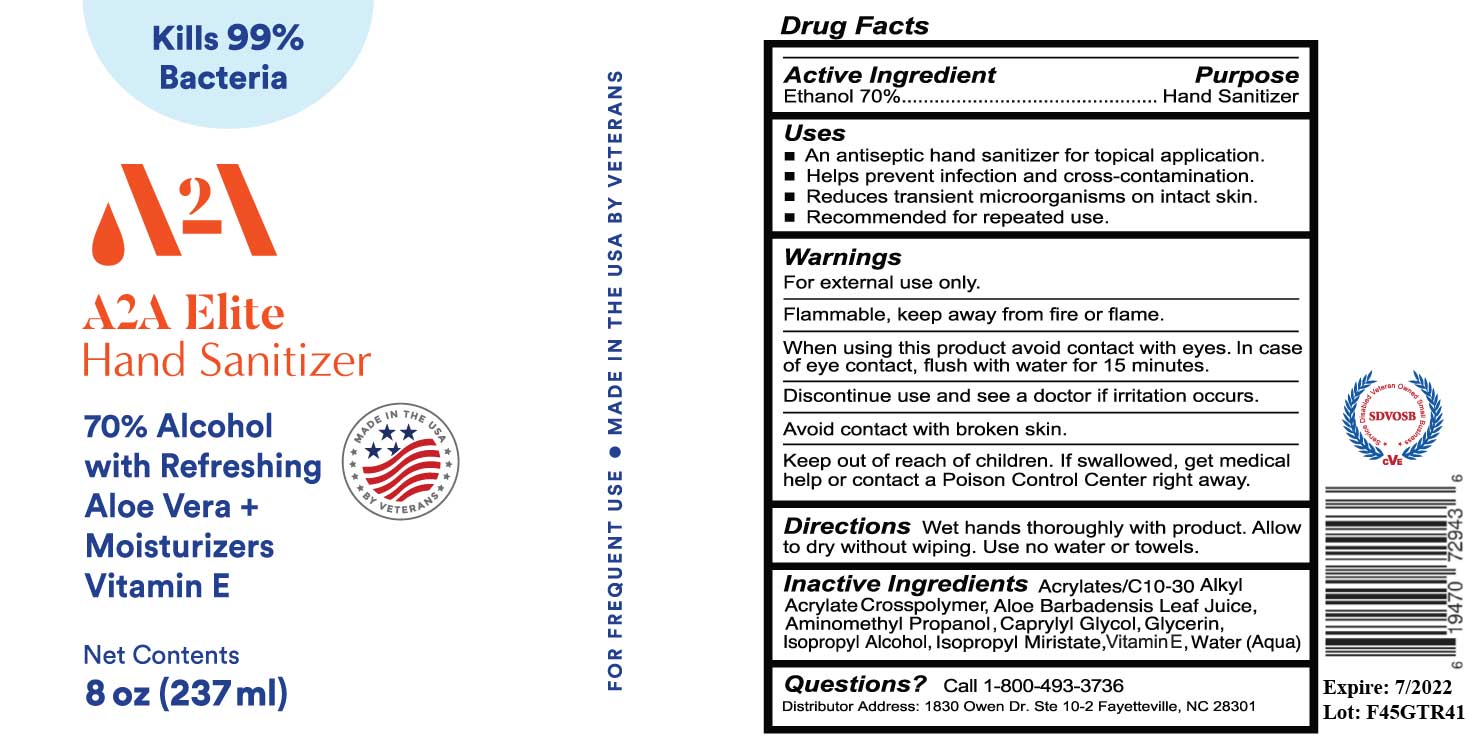 DRUG LABEL: A2A Elite 8oz Gel Hand Sanitizer
NDC: 75321-1308 | Form: GEL
Manufacturer: SunBeam Laboratories LLC
Category: otc | Type: HUMAN OTC DRUG LABEL
Date: 20200813

ACTIVE INGREDIENTS: ALCOHOL 165.61 mL/236.59 mL
INACTIVE INGREDIENTS: CARBOMER INTERPOLYMER TYPE A (ALLYL SUCROSE CROSSLINKED) 7.1 mL/236.59 mL; ISOPROPYL ALCOHOL 0.95 mL/236.59 mL; WATER 62.18 mL/236.59 mL; ISOPROPYL MYRISTATE 0.02 mL/236.59 mL; ALOE VERA LEAF 0.02 mL/236.59 mL; .ALPHA.-TOCOPHEROL 0.02 mL/236.59 mL; GLYCERIN 0.43 mL/236.59 mL; AMINOMETHYLPROPANOL 0.02 mL/236.59 mL; CAPRYLYL GLYCOL 0.24 mL/236.59 mL

A2A Elite 8 0z Gel Hand Sanitizer

This is a hand sanitizer manufactured according to the Temporary Policy for Preparation of Certain Alcohol-Based Hand Sanitizer Products During the Public Health Emergency (CoViD-19); Guidance for Industry.

The hand sanitizer is manufactured using only the following United States Pharmacopoeia (USP) grade ingredients in the preparation of the product (percentage in final product formulation) consistent with World Health Organization (WHO) recommendations:

1. Alcohol (ethanol) (USP or Food Chemical Codex (FCC) grade) (70%, volume/volume (v/v)) in an aqueous solution denatured according to Alcohol and Tobacco Tax and Trade Bureau regulations in 27 CFR part 20.
2. Water (26.28% v/v),
3. Alkyl Acrylate (3.00% v/v).,
4. Isopropyl Alcohol (0.4% v/v),
5. Glycerin (0.18% v/v),
6. Aminomethyl Propanol (0.01% v/v),
7. Glycol (0.10% v/v),
8. Isopropyl Miristrate (0.01% v/v),
9. Aloe (0.01% v/v),
10. Vitamin E (0.01% v/v).

Active Ingredient(s)

Alcohol 70% v/v. Purpose: Antiseptic

Purpose

Antiseptic, Hand Sanitizer

Use

Hand Sanitizer to help reduce bacteria that potentially can cause disease. For use when soap and water are not available.

Warnings

For external use only. Flammable. Keep away from heat or flame

Do not use

- in children less than 2 months of age
- on open skin wounds

When using this product keep out of eyes, ears, and mouth. In case of contact with eyes, rinse eyes thoroughly with water.
Stop use and ask a doctor if irritation or rash occurs. These may be signs of a serious condition.
Keep out of reach of children. If swallowed, get medical help or contact a Poison Control Center right away.

Stop use and ask a doctor if irritation or rash occurs. These may be signs of a serious condition.

Keep out of reach of children. If swallowed, get medical help or contact a Poison Control Center right away.

Directions

- Place enough product on hands to cover all surfaces. Rub hands together until dry.
- Supervise children under 6 years of age when using this product to avoid swallowing.

Other information

- Store between 15-30C (59-86F)
- Avoid freezing and excessive heat above 40C (104F)

Inactive ingredients

Water (26.28% v/v), Alkyl Acrylate (3.00% v/v)., Isopropyl Alcohol (0.4% v/v), Glycerin (0.18% v/v), Aminomethyl Propanol (0.01% v/v), Glycol (0.10% v/v), Isopropyl Miristrate (0.01% v/v), Aloe (0.01% v/v), Vitamin E (0.01% v/v).

Package Label - Principal Display Panel

236.59 mL NDC: 75321-1308-5